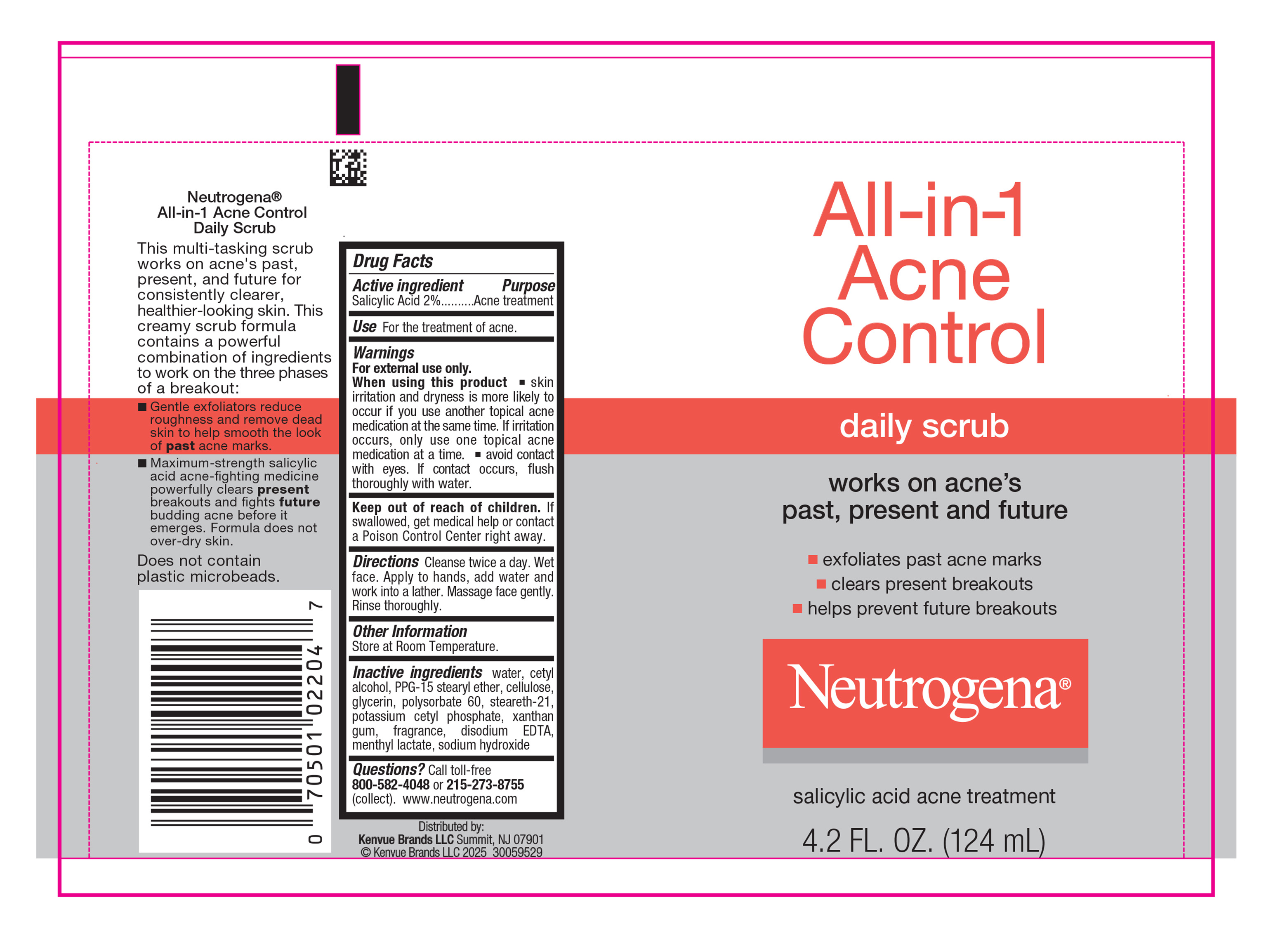 DRUG LABEL: Neutrogena All in 1 Acne Control Daily Scrub
NDC: 69968-0092 | Form: LIQUID
Manufacturer: Kenvue Brands LLC
Category: otc | Type: HUMAN OTC DRUG LABEL
Date: 20250408

ACTIVE INGREDIENTS: SALICYLIC ACID 20 mg/1 mL
INACTIVE INGREDIENTS: WATER; CETYL ALCOHOL; PPG-15 STEARYL ETHER; POWDERED CELLULOSE; STEARETH-21; POLYSORBATE 60; POTASSIUM CETYL PHOSPHATE; XANTHAN GUM; EDETATE DISODIUM; MENTHYL LACTATE, (-)-; SODIUM HYDROXIDE; GLYCERIN

Neutrogena® All-in-1 Acne Control daily scrub

Drug Facts

Active ingredient

Salicylic Acid 2%

Purpose

Acne treatment

Use

For the treatment of acne.

Warnings

For external use only.

When using this product

- skin irritation and dryness is more likely to occur if you use another topical acne medication at the same time. If irritation occurs, only use one topical acne medication at a time.
- avoid contact with eyes. If contact occurs, flush thoroughly with water

Keep out of reach of children. If swallowed, get medical help or contact a Poison Control Center right away.

Directions

Cleanse twice a day. Wet face. Apply to hands, add water and work into a lather. Massage face gently. Rinse thoroughly.

Other Information

Store at Room Temperature.

Inactive ingredients

water, cetyl alcohol, PPG-15 stearyl ether, cellulose, glycerin, Polysorbate 60, steareth-21, potassium cetyl phosphate, xanthan gum, fragrance, disodium EDTA, menthyl lactate, sodium hydroxide

Questions?

Call toll- free 800-582-4048 or 215-273-8755 (collect). www.neutrogena.com

Distributed by:
Kenvue Brands LLC
Summit, NJ 07901

PRINCIPAL DISPLAY PANEL - 124 mL Tube Label

All-in-1

Acne

Control

daily scrub

works on acne's
past, present & future

- exfoliates past acne marks
- clears present breakouts
- helps prevent future breakouts

Neutrogena®

salicylic acid acne treatment

4.2 FL. OZ. (124mL)